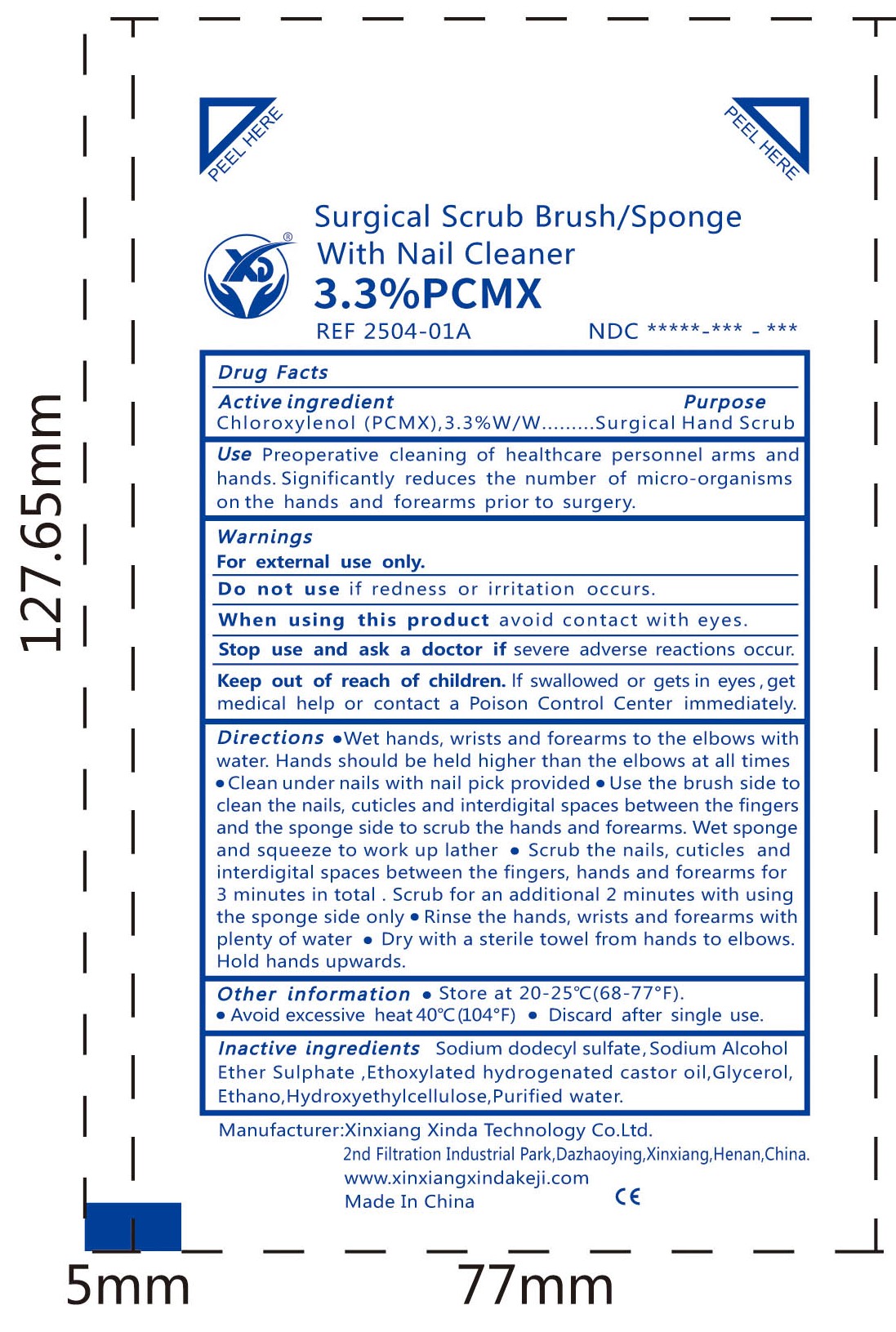 DRUG LABEL: Surgical Scrub Brush/Sponge With Nail Cleaner 3.3% PCMX
NDC: 84128-004 | Form: SPONGE
Manufacturer: Xinxiang Xinda Technology Co.,Ltd
Category: otc | Type: HUMAN OTC DRUG LABEL
Date: 20260108

ACTIVE INGREDIENTS: CHLOROXYLENOL 3.3 g/100 mL
INACTIVE INGREDIENTS: SODIUM LAURYL SULFATE; POLYOXYL 40 HYDROGENATED CASTOR OIL; ALCOHOL; SODIUM LAURETH-5 SULFATE; WATER; HYDROXYETHYL CELLULOSE, UNSPECIFIED; GLYCERIN

84128-004

Active ingredient

Chloroxylenol (pcmx), 3.3% w/w

Purpose

Surgical Hand Scrub

Use

Preoperative cleaning of healthcare personnel arms and hands.Significantly reduces the number of micro-organisms on the hands and forearms prior to surgery.

Warnings

For external use only.

Do not use

if redness or irritation occurs.

When using this product

avoid contact with eyes.

Stop use and ask a doctor if

severe adverse reactions occur.

Keep out of reach of children.

If swallowed or gets in eyes,get medical help or contact a Poison Control Center immediately.

Directions

●Wet hands, wrists and forearms to the elbows with water. Hands should be held higher than the elbows at all times

●Clean under nails with nail pick provided

●Use the brush side toclean the nails, cuticles and interdigital spaces between the fingersand the sponge side to scrub the hands and forearms. Wet sponge and squeeze to work up lather ·

●Scrub the nails, cuticles and interdigital spaces between the fingers, hands and forearms for 3 minutes in total . Scrub for an additional 2 minutes with using the sponge side only

●Rinse the hands, wrists and forearms with plenty of water

●Dry with a sterile towel from hands to elbows.Hold hands upwards.

Inactive ingredients

Ethano, Sodium dodecyl sulfate, Sodium Alcohol Ether Sulphate, Glycerol, Ethoxylated hydrogenated castor oil, Purified Water, Hydroxyethylcellulose

Other information

● Store at 20-25° (68-77°F).
● Avoid overheating 40°C (104 F)
● Discard after single use.